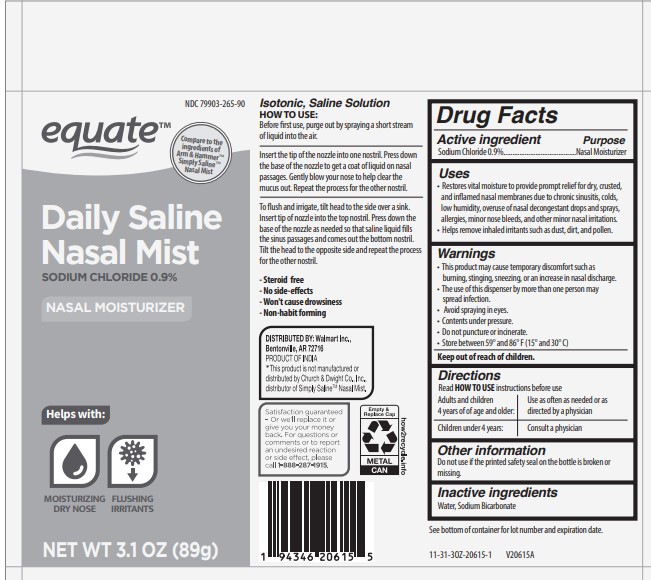 DRUG LABEL: EQUATE DAILY SALINE
NDC: 79903-265 | Form: AEROSOL, SPRAY
Manufacturer: Walmart Stores, Inc.
Category: otc | Type: HUMAN OTC DRUG LABEL
Date: 20260119

ACTIVE INGREDIENTS: SODIUM CHLORIDE 0.9 g/100 mL
INACTIVE INGREDIENTS: WATER; SODIUM BICARBONATE

Active ingredient

Sodium Chloride 0.9%

Purpose

Nasal Moisturizer

Uses

- Restores vital moisture to provide prompt relief for dry, crusted, and inflamed nasal membranes due to chronic sinusitis, colds, low humidity, overuse of nasal decongestant drops and sprays, allergies, minor nose bleeds, and other minor nasal irritations.
- Helps remove inhaled irritants such as dust, dirt, and pollen.

Warnings

- This product may cause temporary discomfort such as burning, stinging, sneezing, or an increase in nasal discharge.
- The use of this dispenser by more than one person may spread infection.
- Avoid spraying in eyes.
- Content under pressure.
- Do not puncture or incinerate.
- Store between 59º and 86º F (15º and 30º C)

Directions

Read HOW TO USE instructions before use

- Adults and children 4 years of age an older: Use as often as needed or as directed by a physician
- Children under 4 years: Consult a physician.

Other information

Do not use if the printed safety seal on the bottle is broken or missing.

Inactive ingredients

Purified Water, Sodium Bicarbonate